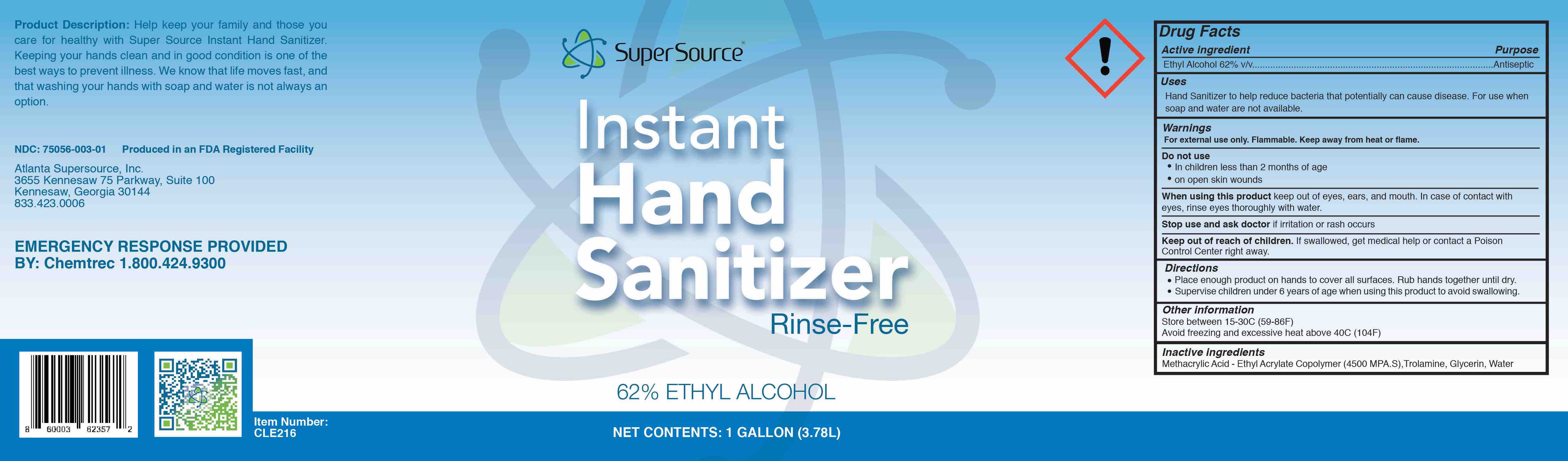 DRUG LABEL: Hand Sanitizer
NDC: 75056-003 | Form: GEL
Manufacturer: Atlanta Supersource, Inc.
Category: otc | Type: HUMAN OTC DRUG LABEL
Date: 20221205

ACTIVE INGREDIENTS: ALCOHOL 62 mL/100 mL
INACTIVE INGREDIENTS: TROLAMINE 0.6 mL/100 mL; GLYCERIN 1 mL/100 mL; METHACRYLIC ACID - ETHYL ACRYLATE COPOLYMER (4500 MPA.S) 5 mL/100 mL; WATER 31.4 mL/100 mL

Hand Sanitizer Gel - Ethyl

Rinse-Free

Product Description: Help keep your family and those you care for healthy with Super Source Instant Hand Sanitizer. Keeping your hands clean and in good condition is one of the best ways to prevent illness. We know that life moves fast, and that washing your hands with soap and water is not always an option.

NDC: 75056-002-03 Produced in an FDA Registered Facility

Atlanta Supersource, Inc.

3655 Kennesaw 75 PKWY, Suite 100

Kennesaw, GA 30144

833.423.0006

EMERGENCY RESPONSE PROVIDED BY: Chemtrec 1.800.424.9300

Active Ingredient(s)

Ethyl Alcohol 62% v/v.

Purpose

Antiseptic

Use

Hand Sanitizer to help reduce bacteria that potentially can cause disease. For use when soap and water are not available.

Warnings

For external use only. Flammable. Keep away from heat or flame

Do not use

- in children less than 2 months of age
- on open skin wounds

When using this product keep out of eyes, ears, and mouth. In case of contact with eyes, rinse eyes thoroughly with water.

Stop use and ask a doctor if irritation or rash occurs. These may be signs of a serious condition.

Keep out of reach of children. If swallowed, get medical help or contact a Poison Control Center right away.

Directions

- Place enough product on hands to cover all surfaces. Rub hands together until dry.
- Supervise children under 6 years of age when using this product to avoid swallowing.

Other information

- Store between 15-30C (59-86F)
- Avoid freezing and excessive heat above 40C (104F)

Inactive ingredients

Methacrylic Acid - Ethyl Acrylate Copolymer (4500 MPA.S), Trolamine, Glycerin, Water

Package Label - Principal Display Panel

Net Contents: 1 Gallon (3.78L) mL NDC: 75053-003-01